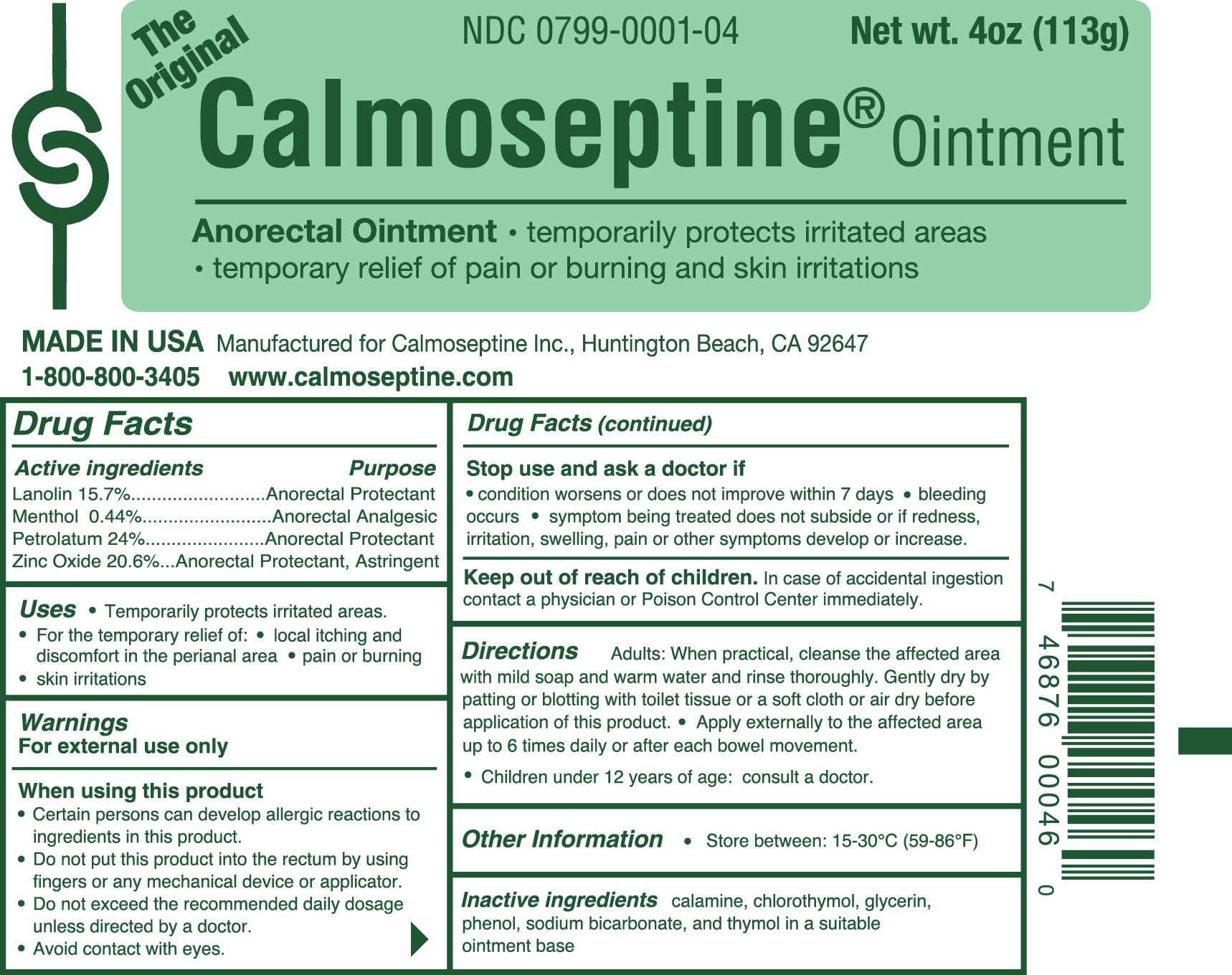 DRUG LABEL: Calmoseptine
NDC: 0799-0001 | Form: OINTMENT
Manufacturer: Calmoseptine Inc.
Category: otc | Type: HUMAN OTC DRUG LABEL
Date: 20250113

ACTIVE INGREDIENTS: LANOLIN 15.7 g/100 g; MENTHOL 0.44 g/100 g; PETROLATUM 24 g/100 g; ZINC OXIDE 20.6 g/100 g
INACTIVE INGREDIENTS: FERRIC OXIDE RED; CHLOROTHYMOL; GLYCERIN; PHENOL; SODIUM BICARBONATE; THYMOL

Calmoseptine Ointment

Active Ingredients

Lanolin 15.7%

Menthol 0.44%

Petrolatum 24%

Zinc Oxide 20.6%

Purpose

Active Ingredients Purpose
Lanolin 15.7%...........................Anorectal Protectant
Menthol 0.44%...........................Anorectal Analgesic
Petrolatum 24%........................Anorectal Protectant
Zinc Oxide 20.6%......Anorectal Protectant, Astringent

Uses

- Temporarily protects irritated areas.
- For the temporary relief of:
- local itching and discomfort in the perianal area
- pain or burning
- skin irritations

Warnings

For external use only

When using this product

* Certain persons can develop allergic reactions to ingredients in this product.
* Do not put this product into the rectum by using fingers or any mechanical device or applicator.
* Do not exceed the recommended daily dosage unless directed by a doctor.
* Avoid contact with eyes.

Stop use and ask doctor if

- condition worsens or does not improve within 7 days
- bleeding occurs
- symptom being treated does not subside or if redness, irritation, swelling, pain or other symptoms develop or increase.

Keep out of reach of children.

In case of accidental ingestion contact a physician or Poison Control Center immediately.

Directions

Adults: When practical, cleanse the affected area with mild soap and warm water and rinse thoroughly.
Gently dry by patting or blotting with toilet tissue or a soft cloth or air dry before application of this product.
Apply externally to the affected area up to 6 times daily or after each bowel movement.
Children under 12 years of age: consult a doctor.

Inactive Ingredients:

calamine, chlorothymol, glycerin, phenol,

sodium bicarbonate, and thymol in a suitable ointment base